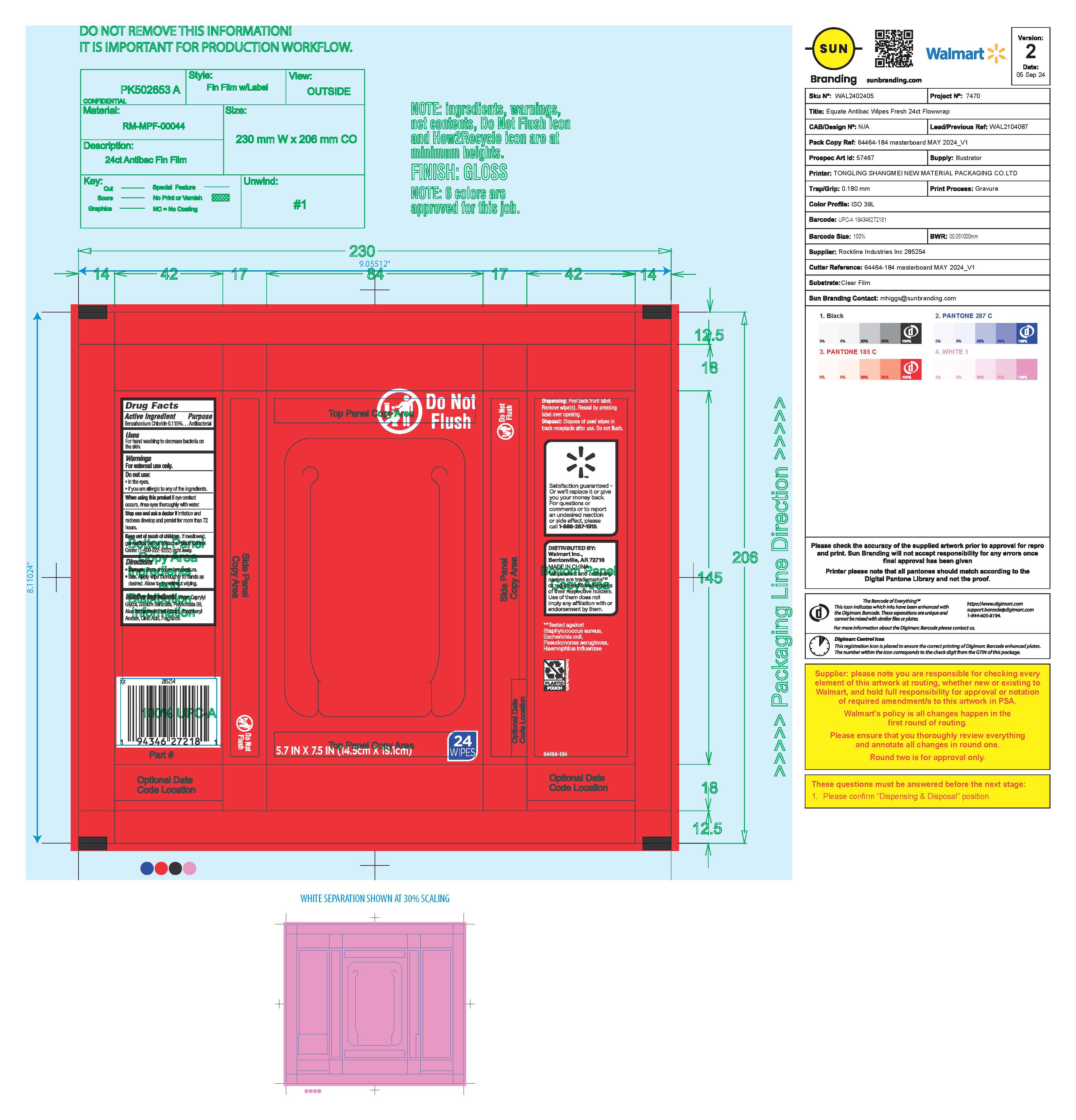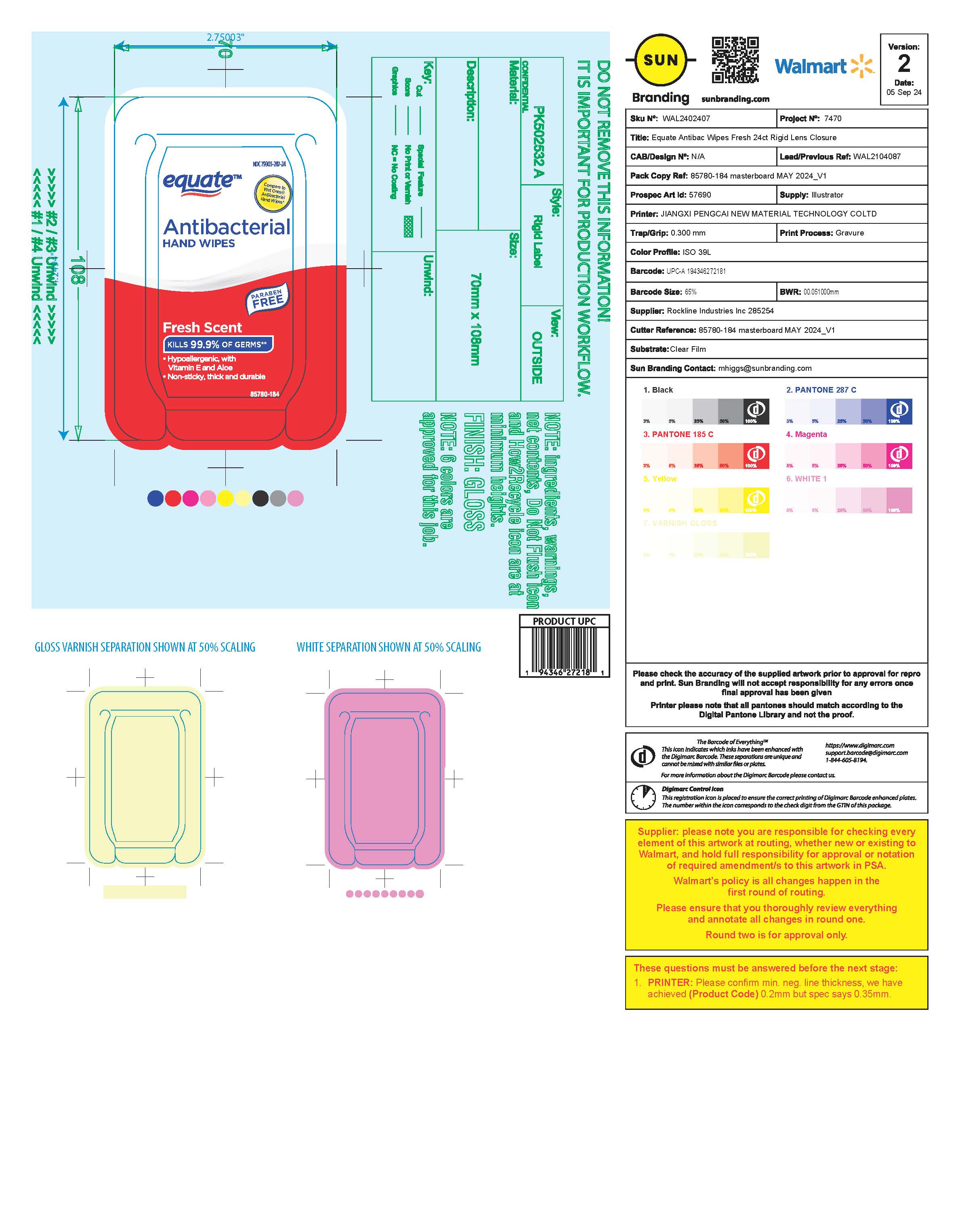 DRUG LABEL: Equate Antibacterial Wipes Fresh
NDC: 79903-287 | Form: CLOTH
Manufacturer: Walmart, Inc.
Category: otc | Type: HUMAN OTC DRUG LABEL
Date: 20251001

ACTIVE INGREDIENTS: BENZALKONIUM CHLORIDE 0.115 g/1 1
INACTIVE INGREDIENTS: SODIUM BENZOATE; CAPRYLYL GLYCOL; POLYSORBATE 20; WATER; ALOE VERA LEAF; .ALPHA.-TOCOPHEROL ACETATE; CITRIC ACID MONOHYDRATE

Equate Antibacterial Hand Wipes Fresh

Active Ingredient

Benzalkonium Chloride 0.115%

Purpose

Antibacterial

Uses

For handwashing to decrease bacteria on the skin

Warnings

For external use only

Do not use

- In the eyes
- If you are allergic to any of the ingredients

When using this product

if eye contact occurs, rinse eyes thoroughly with water.

Stop use and ask a doctor

If irritation and redness develops and persist for more than 72 hours.

Keep out of reach of children

if swallowed get medical help or contact a Poison Control Center (1-800-222-1222) right away.

Directions

- Storage, Store at room temperature
- Use. Apply wipe thoroughly to hands as desired. Allow to dry without wiping.

Inactive ingredients

Water, Caprylyl Glycol, Sodium Benzoate, Polysorbate 20, Aloe Barbadensis Leaf Extract, Tocopheryl Acetate, Citric Acid, Fragrance